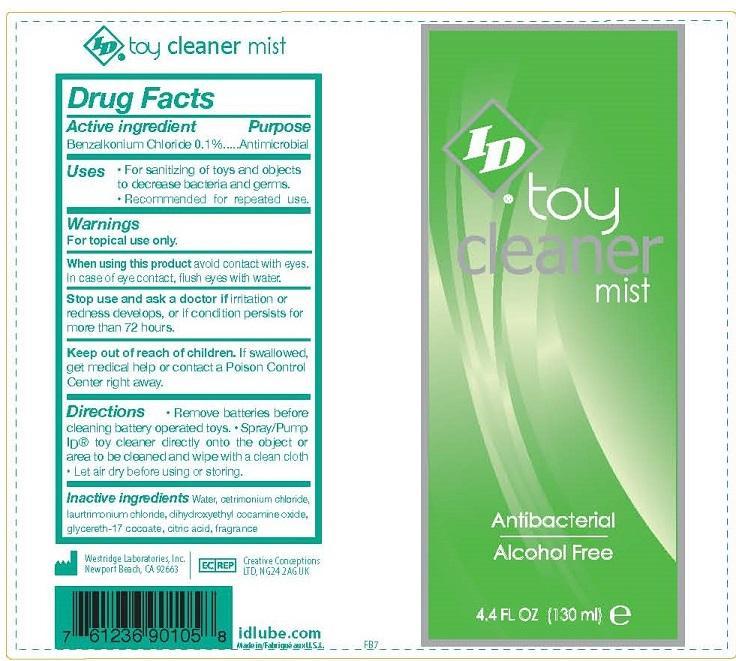 DRUG LABEL: TOY CLEANER MIST
NDC: 61856-101 | Form: SPRAY
Manufacturer: WESTRIDGE LABORATORIES INC
Category: otc | Type: HUMAN OTC DRUG LABEL
Date: 20140129

ACTIVE INGREDIENTS: BENZALKONIUM CHLORIDE 0.1 g/100 mL
INACTIVE INGREDIENTS: WATER; CETRIMONIUM CHLORIDE; LAURTRIMONIUM CHLORIDE; DIHYDROXYETHYL COCAMINE OXIDE; GLYCERETH-17 COCOATE; ANHYDROUS CITRIC ACID

ACTIVE INGREDIENT

BENZALKONIUM CHLORIDE 0.1%

PURPOSE

ANTIMICROBIAL

USES

- FOR SANITIZING OF TOYS AND OBJECTS TO DECREASE BACTERIA AND GERMS.
- RECOMMENDED FOR REPEATED USE.

WARNINGS

WRNINGS

FOR TOPICAL USE ONLY

When using this product avoid contact with eyes. In case of eye contact, flush eyes with water

Stop use and ask a doctor if irritation or redness develops, or if condition persists for more than 72 hours.

Keep out of reach of children. If swallowed, get medical help or contact a Poison Control Center right away.

Directions

- Remove batteries beforecleaning battery operated toys.
- Spray/Pump ID® toy cleaner directly onto the object or area to be cleaned and wipe with a clean cloth
- Let air dry before using or storing.

Inactive ingredients

Water, cetrimonium chloride, laurtrimonium chloride, dihydroxyethyl cocamine oxide, glycereth-17 cocoate, citric acid, fragrance